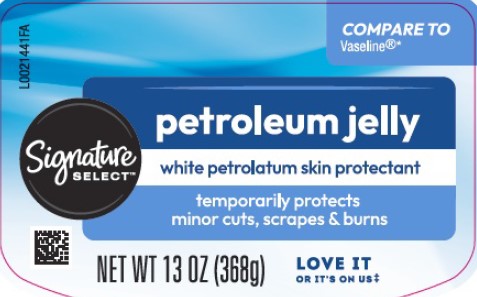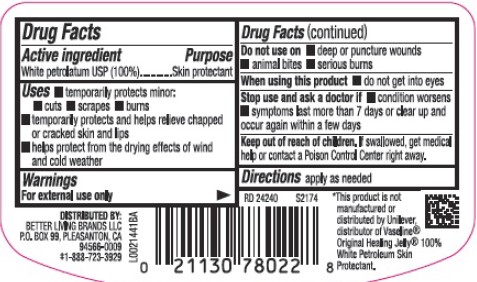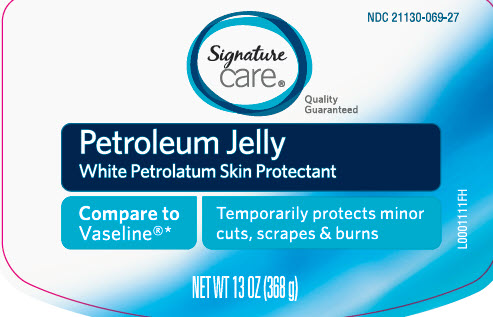 DRUG LABEL: Pure petroleum
NDC: 21130-069 | Form: JELLY
Manufacturer: Better Living Brands, LLC
Category: otc | Type: HUMAN OTC DRUG LABEL
Date: 20260223

ACTIVE INGREDIENTS: PETROLATUM 1 g/1 g

Signature Care_Signature Select 069.001/069AA
Petroleum Jelly

Active ingredient

White Petrolatum USP (100%)

Purpose

Skin protectant

Uses

- temporarily protects minor: cuts, scrapes, burns
- temporarily protects and helps relieve chapped or cracked skin and lips
- helps protect from the drying effects of wind and cold weather

Warnings

For external use only

Do not use

- deep or puncture wounds
- animal bites
- serious burns

When using this product

- do not get into eyes

Stop use and ask a doctor if

- condition worsens
- symptoms last more than 7 days or clear up and occur again within a few days

Keep out of reach of children.

If swallowed, get medical help or contact a Poison Control Center right away.

Directions

apply as needed

inactive ingredients

none

Adverse Reactions

DISTRIBUTED BY BETTER LIVING BRANDS, LLC

P.O. BOX 99, PLEASATON, CA 94566-0009

‡1-888-723-3929

Disclaimer

*This product is not manufactured or distributed by Unilever, distributor of Vaseline Original Healing Jelly 100% White Petroleum Skin Protectant.

principal display panel

NDC 21130-069-27

Signature care

Quality Guaranteed

Petroleum Jelly

White Petrolatum Skin Protectant

Compare to Vaseline*

Temporarily protects minor cuts, scrapes & burns

NET WT 13 OZ (368 g)

principal display panel

COMPARE TO Vaseline®*

Signature SELECT™

petroleum jelly

white petrolatum skin protectant

temporarily protects minor cuts, scrapes & burns

NET WT 13 OZ (368g)

LOVE IT OR IT'S ON US‡